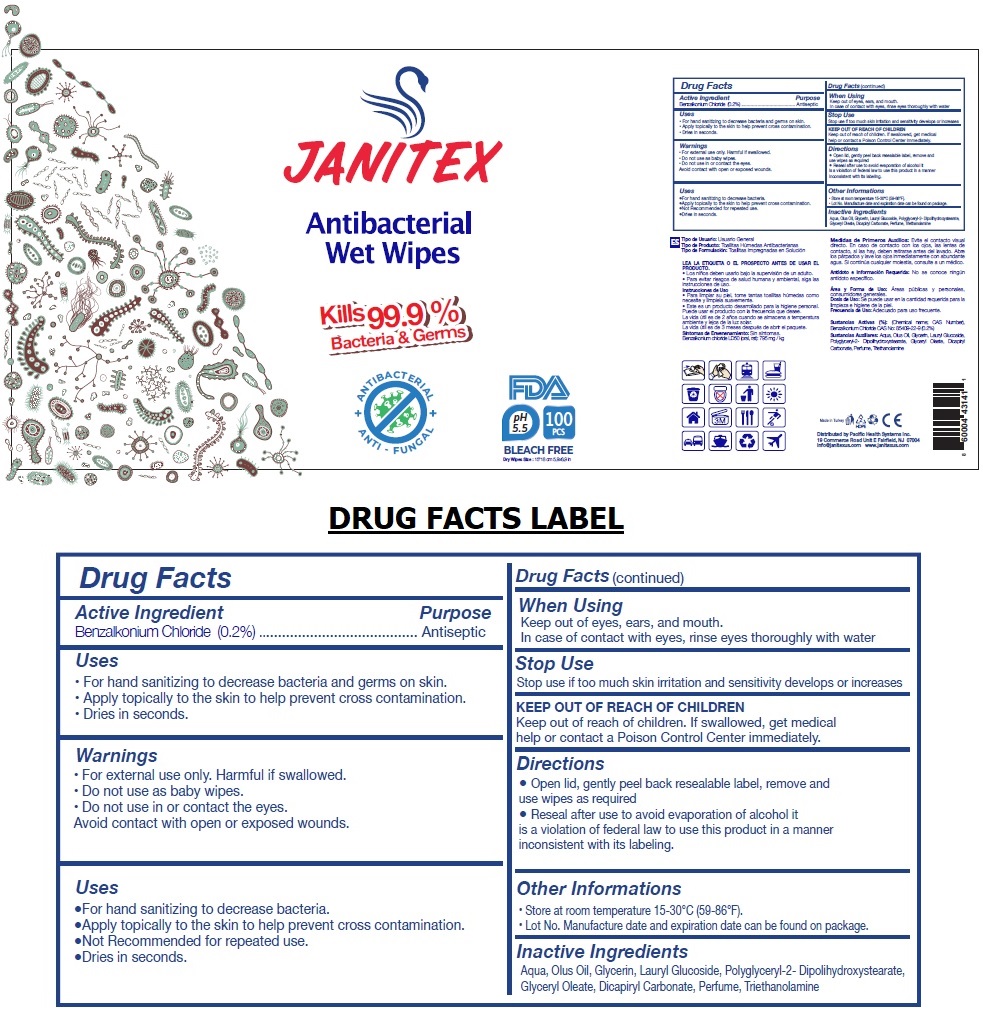 DRUG LABEL: JANITEX ANTIBACTERIAL WET WIPES
NDC: 79519-010 | Form: CLOTH
Manufacturer: Pacific Health Systems Inc.
Category: otc | Type: HUMAN OTC DRUG LABEL
Date: 20200714

ACTIVE INGREDIENTS: BENZALKONIUM CHLORIDE 0.2 g/100 mL
INACTIVE INGREDIENTS: WATER; CORN OIL; GLYCERIN; LAURYL GLUCOSIDE; POLYGLYCERYL-2 DIPOLYHYDROXYSTEARATE; GLYCERYL OLEATE; DICAPRYLYL CARBONATE; TROLAMINE

JANITEX Antibacterial Wet Wipes

Active Ingredient

Benzalkonium Chloride (0.2%)

Purpose

Antiseptic

Uses

● For hand sanitizing to decrease bacteria and germs on skin.

● Apply topically to the skin to help prevent cross contamination.

● Not Recommended for repeated use.

● Dries in seconds.

Warnings

• For external use only. Harmful if swallowed.

• Do not use as baby wipes.

• Do not use in or contact the eyes.

Avoid contact with open or exposed wounds.

When Using

Keep out of eyes, ears, and mouth.

In case of contact with eyes, rinse eyes thoroughly with water

Stop Use

Stop use if too much skin irritation and sensitivity develops or increases

Keep out of reach of children. If swallowed, get medical help or contact a Poison Control Center immediately.

Directions

● Open lid, gently peel back resealable label, remove and use wipes as required

● Reseal after use to avoid evaporation of alcohol it is a violation of federal law to use this product in

a manner inconsistent with its labeling.

Other Informations

• Store at room temperature 15-30℃ (59-86°F).

• Lot No. Manufacture date and expiration date can be found on package.

Inactive Ingredients

Aqua, Olus Oil, Glycerin, Lauryl Glucoside, Polyglyceryl-2- Dipolihydroxystearate, Glyceryl Oleate,

Dicapiryl Carbonate, Perfume, Triethanolamine

Kills 99.9% Bacteria & Germs

ANTIBACTERIAL

ANTI - FUNGAL

pH 5.5

BLEACH FREE

Made in Turkey

Distributed by Pacific Health Systems Inc.

19 Commerce Road Unit E Fairfield, NJ 07004

info@janitexus.com www.janitexus.com